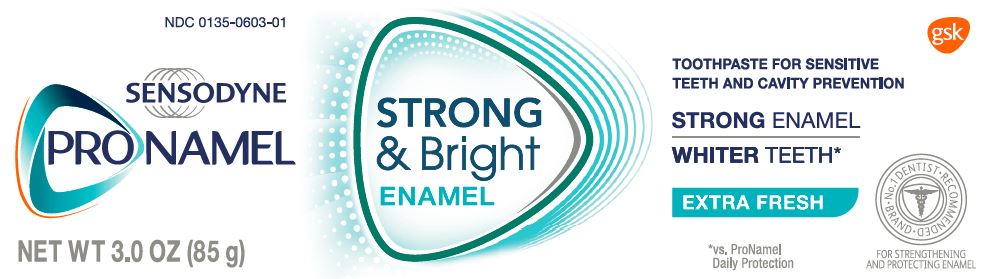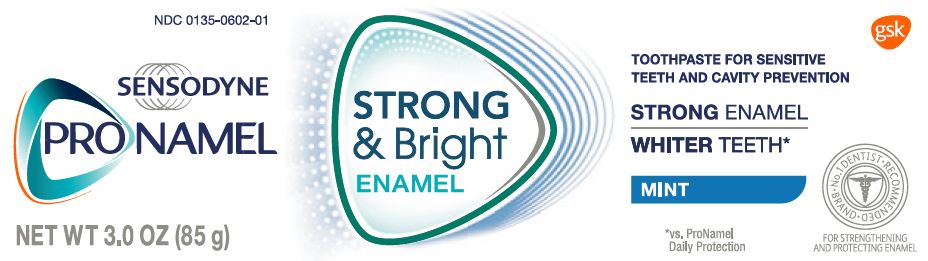 DRUG LABEL: Sensodyne Pronamel
NDC: 0135-0602 | Form: PASTE
Manufacturer: Haleon US Holdings LLC
Category: otc | Type: HUMAN OTC DRUG LABEL
Date: 20240306

ACTIVE INGREDIENTS: POTASSIUM NITRATE 50 mg/1 g; SODIUM FLUORIDE 1.15 mg/1 g
INACTIVE INGREDIENTS: WATER; HYDRATED SILICA; SORBITOL; GLYCERIN; POLYETHYLENE GLYCOL 400; COCAMIDOPROPYL BETAINE; TITANIUM DIOXIDE; XANTHAN GUM; SACCHARIN SODIUM; SODIUM HYDROXIDE

Drug Facts

Active ingredients

Potassium nitrate 5%

Sodium fluoride 0.25% (0.15% w/v fluoride ion)

Purpose

Antihypersensitivity

Anticavity

Uses

- builds increasing protection against painful sensitivity of the teeth to cold, heat, acids, sweets, or contact.
- aids in the prevention of dental cavities.

Warnings

When using this product,

if irritation occurs discontinue use.

Stop use and ask a dentist if

- the problem persists or worsens. Sensitive teeth may indicate a serious problem that may need prompt care by a dentist.
- pain/sensitivity still persists after 4 weeks of use.

Keep out of reach of children.

If more than used for brushing is accidentally swallowed, get medical help or contact a Poison Control Center right away.

Directions

Adults and children 12 years of age and older: | Apply at least a 1-inch strip of the product onto a soft bristle toothbrush. Brush teeth thoroughly for at least 1 minute twice a day (morning and evening), and not more than 3 times a day, or as recommended by a dentist or doctor. Make sure to brush all sensitive areas of the teeth. Minimize swallowing. Spit out after brushing.
Children under 12 years | Consult a dentist or doctor.

Other information

store below 25°C (77°F)

Inactive ingredients

water, hydrated silica, sorbitol, glycerin, PEG-8, flavor, cocamidopropyl betaine, titanium dioxide, xanthan gum, sodium saccharin, sodium hydroxide

Questions or comments?

Call toll-free 1-866-844-2797

Principal Display Panel

NDC 0135-0602-01

SENSODYNE

PRONAMEL

STRONG & Bright

ENAMEL

TOOTHPASTE FOR SENSITIVE TEETH AND CAVITY PREVENTION

STRONGENAMEL

WHITERTEETH*

MINT

No. 1 DENTIST RECOMMENDED BRAND

FOR STRENGTHENING AND PROTECTING ENAMEL

*vs. ProNamel Daily Protection

NET WT 3.0 OZ (85 g)

Enamel is the vital layer of protection for your teeth and keeping it strong is so important.

Sensodyne ProNamel STRONG & BrightENAMEL gives you whiter teeth* while actively helping to strengthen your tooth enamel and protect against everyday acids.

*vs. ProNamel Daily Protection

With twice daily brushing, the dual action formulation:

- Delivers minerals into the enamel to help STRENGTHEN & PROTECT.
- Polishes away stains for WHITER BRIGHTER TEETH.

FRESHENSbreath and fights CAVITIES

GSKConsumer Healthcare

Warren, NJ 07059

Trademarks are owned by or licensed to the GSK group of companies.

©2017 GSK group of companies or its licensor

ALWAYS FOLLOW THE LABEL

105491XC

Principal Display Panel

NDC 0135-0603-01

SENSODYNE

PRONAMEL

STRONG & Bright

ENAMEL

TOOTHPASTE FOR SENSITIVE TEETH AND CAVITY PREVENTION

STRONGENAMEL

WHITERTEETH*

EXTRA FRESH

No. 1 DENTIST RECOMMENDED BRAND

FOR STRENGTHENING AND PROTECTING ENAMEL

*vs. ProNamel Daily Protection

NET WT 3.0 OZ (85 g)

Enamel is the vital layer of protection for your teeth and keeping it strong is so important.

Sensodyne ProNamel STRONG & BrightENAMEL gives you whiter teeth* while actively helping to strengthen your tooth enamel and protect against everyday acids.

*vs. ProNamel Daily Protection

With twice daily brushing, the dual action formulation:

- Delivers minerals into the enamel to help STRENGTHEN & PROTECT.
- Polishes away stains for WHITER BRIGHTER TEETH.

FRESHENSbreath and fights CAVITIES

GSKConsumer Healthcare

Warren, NJ 07059

Trademarks are owned by or licensed to the GSK group of companies.

©2017 GSK group of companies or its licensor.

ALWAYS FOLLOW THE LABEL

105488XC